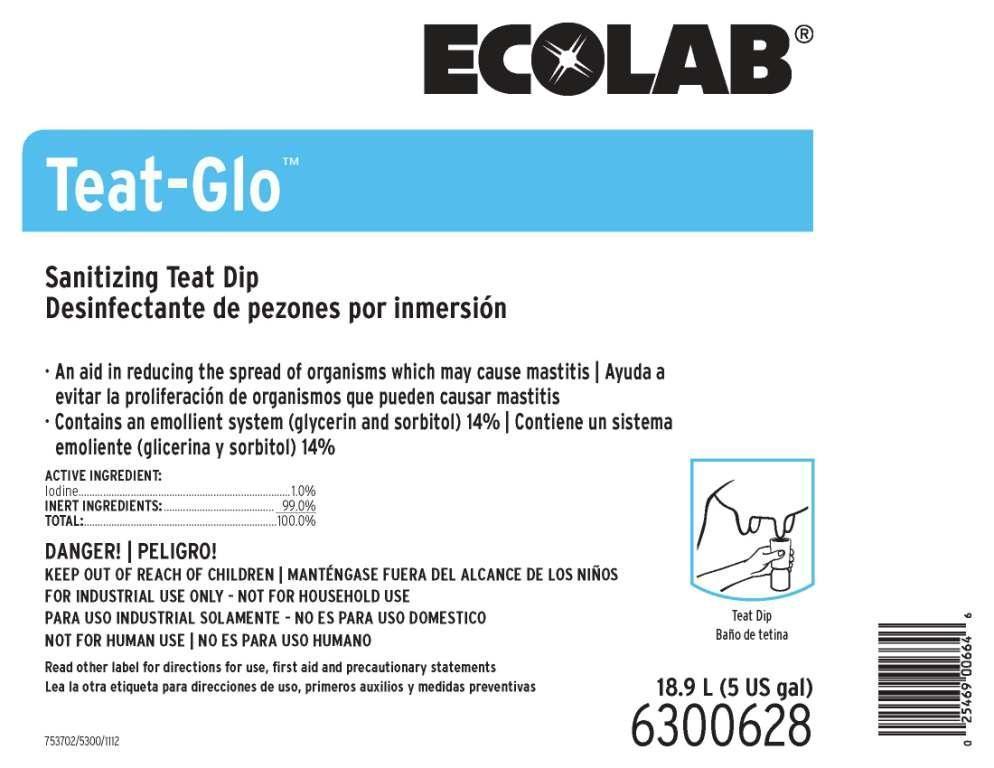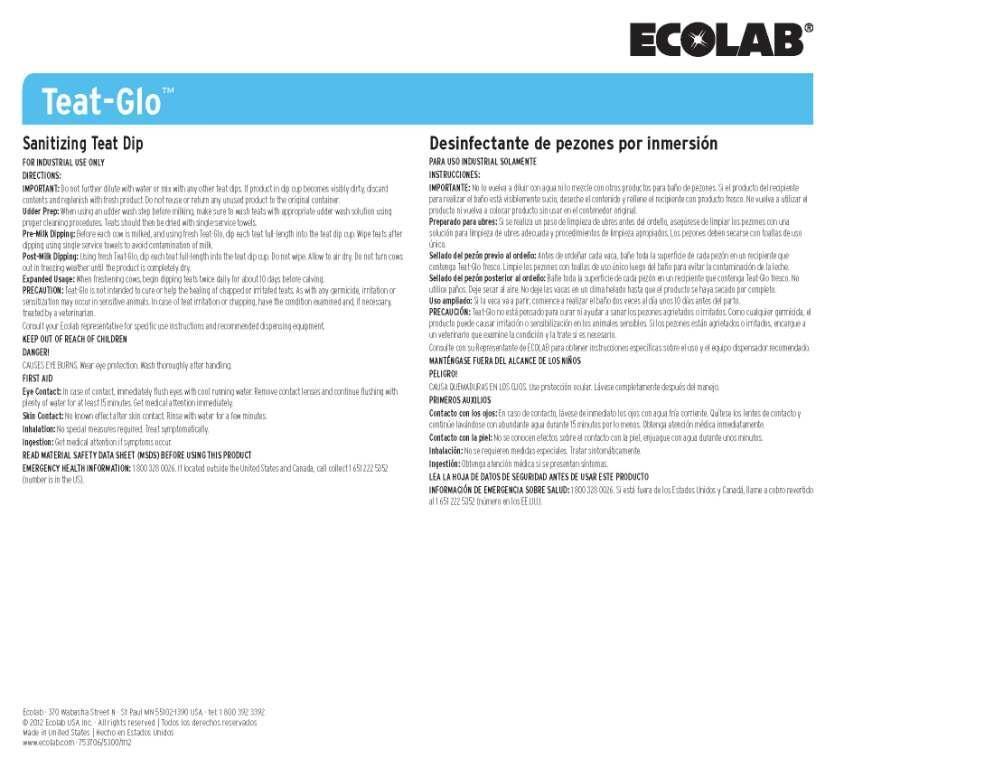 DRUG LABEL: Teat-Glo Teat Dip
NDC: 47593-149 | Form: SOLUTION
Manufacturer: Ecolab Inc.
Category: animal | Type: OTC ANIMAL DRUG LABEL
Date: 20250730

ACTIVE INGREDIENTS: Iodine 10 mg/1 mL
INACTIVE INGREDIENTS: WATER; Sorbitol; Glycerin

SAFE HANDLING WARNING

DANGER!

CAUSES EYE BURNS. Wear eye protection. Wash thoroughly after handling.

KEEP OUT OF REACH OF CHILDREN | FOR INDUSTRIAL USE ONLY - NOT FOR HOUSEHOLD USE

NOT FOR HUMAN USE

Read other label for directions for use, first aid and precautionary statements

DIRECTIONS:

IMPORTANT: Do not further dilute with water or mix with any other teat dips. If product in dip cup becomes visibly dirty, discard contents and replenish with fresh product. Do not reuse or return any unused product to the original container.

Udder Prep: When using an udder wash step before milking, make sure to wash teats with appropriate udder wash solution using proper cleaning procedures. Teats should then be dried with single-service towels.

Pre-Milk Dipping: Before each cow is milked, and using fresh Teat-Glo, dip each teat full-length into the teat dip cup. Wipe teats after dipping using single-service towels to avoid contamination of milk.

Post-Milk Dipping: Using fresh Teat-Glo, dip each teat full-length into the teat dip cup. Do not wipe. Allow to air dry. Do not turn cows out in freezing weather until the product is completely dry.

Expanded Usage: When freshening cows, begin dipping teats twice daily for about 10 days before calving.

PRECAUTION: Teat-Glo is not intended to cure or help the healing of chapped or irritated teats. As with any germicide, irritation or sensitization may occur in sensitive animals. In case of teat irritation or chapping, have the condition examined and, if necessary, treated by a veterinarian.

Consult your Ecolab representative for specific use instructions and recommended dispensing equipment.

OTHER SAFETY INFORMATION

FIRST AID

Eye Contact: In case of contact, immediately flush eyes with cool running water. Remove contact lenses and continue flushing with plenty of water for at least 15 minutes. Get medical attention immediately.

Skin Contact: No known effect after skin contact. Rinse with water for a few minutes.

Inhalation: No special measures required. Treat symptomatically.

Ingestion: Get medical attention if symptoms occur.

READ MATERIAL SAFETY DATA SHEET (MSDS) BEFORE USING THIS PRODUCT

EMERGENCY HEALTH INFORMATION: 1 800 328 0026. If located outside the United States and Canada, call collect 1 651 222 5352 (number is in the US).

Representative label and principal display panel

ECOLAB

Teat-Glo™

Sanitizing Teat Dip

An aid in reducing the spread of organisms which may cause mastitis

Contains an emollient system (glycerin and sorbitol) 14%

ACTIVE INGREDIENT:

Iodine.............................................................................1.0%

INERT INGREDIENTS:......................................... 99.0%

TOTAL:......................................................................100.0%

208 L (55 US gal)

6300630

Ecolab · 370 Wabasha Street N · St Paul MN 55102-1390 USA · tel: 1 800 392 3392

© 2012 Ecolab USA Inc. · All rights reserved | Todos los derechos reservados

Made in United States | Hecho en Estados Unidos

www.ecolab.com · 753706/5300/1112